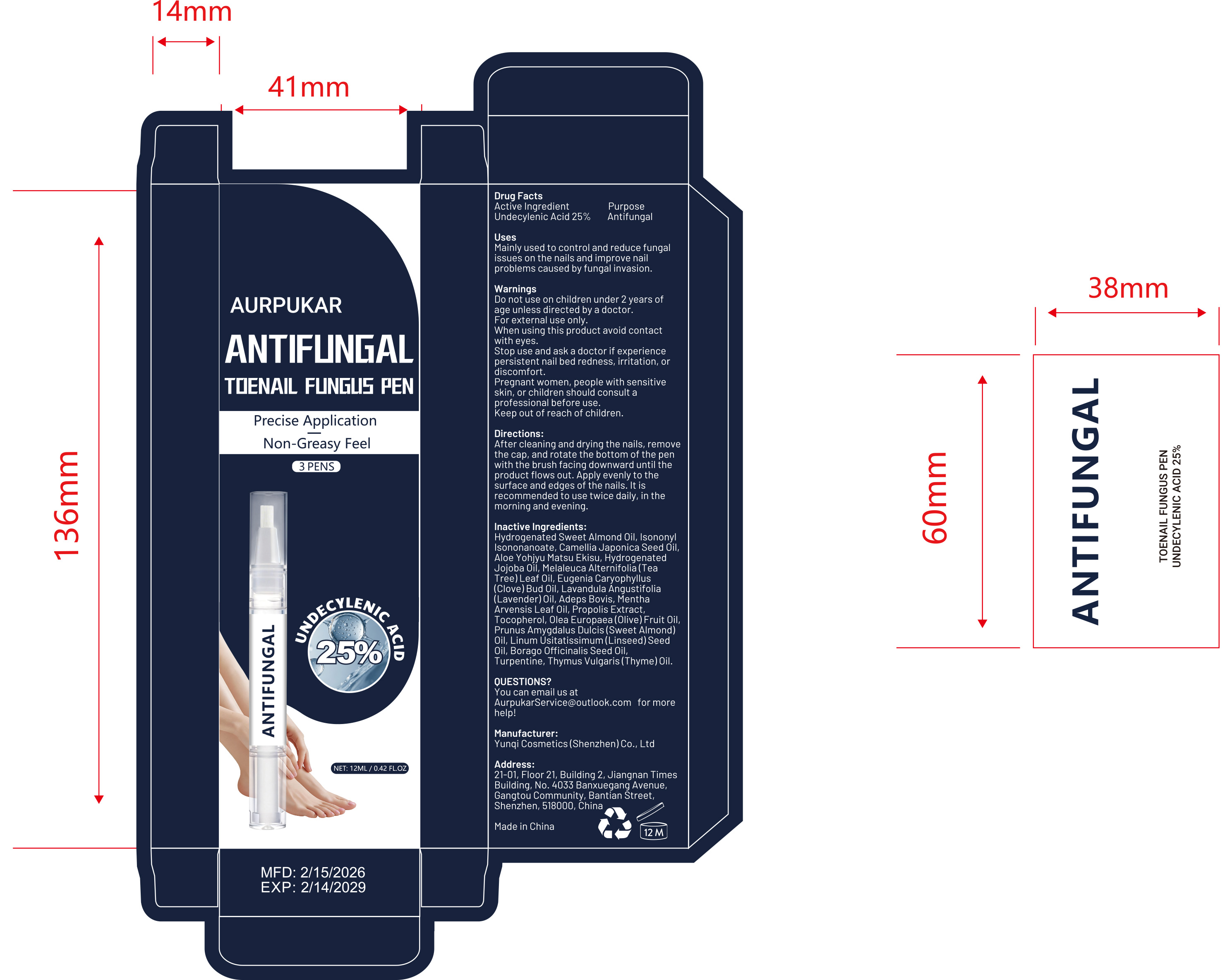 DRUG LABEL: ANTIFUNGAL TOENAIL FUNGUS PEN
NDC: 84763-009 | Form: LIQUID
Manufacturer: Yunqi Cosmetics (Shenzhen) Co., Ltd
Category: otc | Type: HUMAN OTC DRUG LABEL
Date: 20260118

ACTIVE INGREDIENTS: UNDECYLENIC ACID 0.25 g/1 mL
INACTIVE INGREDIENTS: EUGENIA CARYOPHYLLUS (CLOVE) BUD OIL; PROPOLIS WAX; BORAGO OFFICINALIS SEED OIL; THYMUS VULGARIS (THYME) OIL; ADEPS BOVIS; LAVANDULA ANGUSTIFOLIA (LAVENDER) OIL; MENTHA ARVENSIS LEAF OIL; ALOE; ISONONYL ISONONANOATE; TURPENTINE; HYDROGENATED JOJOBA OIL; MELALEUCA ALTERNIFOLIA (TEA TREE) LEAF OIL; CAMELLIA JAPONICA SEED OIL; OLEA EUROPAEA (OLIVE) FRUIT OIL; LINUM USITATISSIMUM (LINSEED) SEED OIL; TOCOPHEROL; PRUNUS AMYGDALUS DULCIS (SWEET ALMOND) OIL

84763-009 ANTIFUNGAL TOENAIL FUNGUS PEN

ACTIVE INGREDIENT

Undecylenic Acid 25%

PURPOSE

Antifungal

INDICATIONS AND USAGE

Mainly used to control and reduce fungalissues on the nails and improve nailproblems caused by fungal invasion.

WARNINGS

For external use only.

Do not use on children under 2 years ofage unless directed by a doctor.

When using this product avoid contactwith eyes.

Stop use and ask a doctorif experience persistent nail bed redness,irritation, or discomfort.
Pregnant women, people with sensitive skin, or children should consult a professional before use.

Keep out of reach of children.

DOSAGE AND ADMINISTRATION

After cleaning and drying the nails, removethe cap, and rotate the bottom of the penwith the brush facing downward until theproduct flows out. Apply evenly to thesurface and edges of the nails. lt isrecommended to use twice daily, in themorning and evening

INACTIVE INGREDIENT

Hydrogenated Sweet Almond Oil, lsononyIsononanoate,Camellia vaponica Seed 0ilAloe Yohiyu Matsu Ekisu, HydrogenatedVojoba Oil, Melaleuca Alternifolia(TeaTree)Leaf Oil, Eugenia Caryophyllus(Clove)Bud 0il, Lavandula Angustifolia(Lavender)0il,Adeps Bovis, MenthaArvensis Leaf Oil, Propolis ExtractTocopherol, Olea Europaea(0live)Fruit 0il.Prunus Amygdalus Dulcis(Sweet Almond)Oil, Linum Usitatissimum(Linseed)SeedOil, Borago Officinalis Seed Oil,Turpentine, Thymus Vulgaris(Thyme)0il